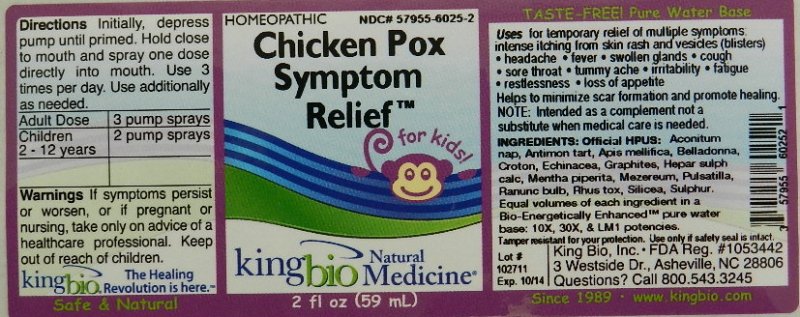 DRUG LABEL: Chicken Pox Symptom Relief
NDC: 57955-6025 | Form: LIQUID
Manufacturer: King Bio Inc.
Category: homeopathic | Type: HUMAN OTC DRUG LABEL
Date: 20111109

ACTIVE INGREDIENTS: ACONITUM NAPELLUS 10 [hp_X]/59 mL; ANTIMONY POTASSIUM TARTRATE 10 [hp_X]/59 mL; APIS MELLIFERA 10 [hp_X]/59 mL; ATROPA BELLADONNA 10 [hp_X]/59 mL; CROTON TIGLIUM SEED 10 [hp_X]/59 mL; GRAPHITE 10 [hp_X]/59 mL; CALCIUM SULFIDE 10 [hp_X]/59 mL; MENTHA PIPERITA 10 [hp_X]/59 mL; DAPHNE MEZEREUM BARK 10 [hp_X]/59 mL; RANUNCULUS BULBOSUS 10 [hp_X]/59 mL; TOXICODENDRON PUBESCENS LEAF 10 [hp_X]/59 mL; PULSATILLA VULGARIS 10 [hp_X]/59 mL; SILICON DIOXIDE 10 [hp_X]/59 mL; SULFUR 10 [hp_X]/59 mL; ECHINACEA ANGUSTIFOLIA 10 [hp_X]/59 mL
INACTIVE INGREDIENTS: WATER

Chicken Pox Symptom Relief

Active Ingredients

HPUS active ingredients

Aconitum Napellus

Antimonium Tartaricum

Apis Mellifica

Belladonna

Croton Tiglium

Echinacea Angustifolia

Graphites

Hepar Sulphuris Calcareum

Mentha Piperita

Mezereum

Ranunculus Bulbosus

Rhus Toxicodendron

Pulsatilla

Silicea

Sulphur

Reference image chicken pox.jpg

Inactive Ingredient

Equal volumes of each ingredient in a Bio-Energetically Enhanced pure water base: 10X, 30X, and LM1 Potencies.

Reference image chicken pox.jpg

Dosage and Administration

Directions Initially, depress pump until primed. Hold close to mouth and spray one dose directly into mouth. Use 3 times per day. Use additionally as needed.

Adult Dose- 3 pump sprays

Children 2 - 12 years- 2 pump sprays

Reference image chicken pox.jpg

Purpose

Uses for temporary relief of multiple symptoms: Intense itching from skin rash and vesicles (blisters), headache, fever, swollen glands, cough, sore throat, tummy ache, irritability, restlessness, fatigue, loss of appetite.

Helps to minimize scar formation and promote healing.

Note: For symptomatic relief only. This product is not intended as a substitute for standard medical care. Contact your physician for guidance in treating chicken pox.

Reference image chicken pox.jpg

Indications and Usage

Uses for temporary relief of multiple symptoms:

- intense itching from skin rash and vesicles (blisters)
- headache
- fever
- swollen glands
- cough
- sore throat
- tummy ache
- irritability
- fatigue
- restlessness
- loss of appetite

Helps to minimize scar formation and promote healing.
Reference image chicken pox.jpg

Warnings

Warnings If symptoms persist or worsen, or if pregnant or nursing, take only on advice of a healthcare professional. Keep out of reach of children.

Tamper resistant for your protection. Use only if safety seal is intact.

Reference image chicken pox.jpg

Keep Out Of Reach Of Children

Reference image chicken pox.jpg

PACKAGE LABEL

King Bio Inc.

3 Westside Dr.

Asheville, NC 28806

Questions? Call 800.543.3245

www.kingbio.com

Reference image chicken pox.jpg